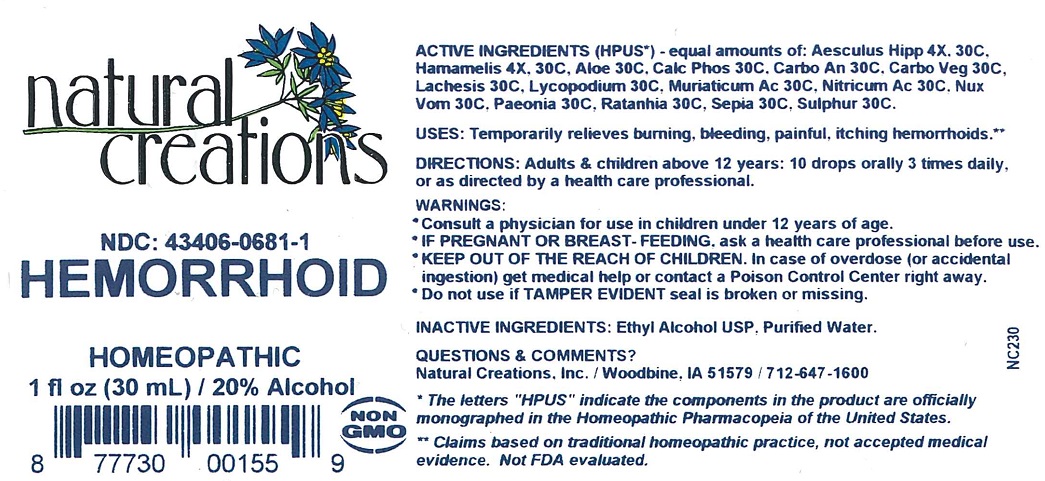 DRUG LABEL: Hemorrhoid
NDC: 43406-0681 | Form: LIQUID
Manufacturer: Natural Creations, Inc
Category: homeopathic | Type: HUMAN OTC DRUG LABEL
Date: 20251216

ACTIVE INGREDIENTS: HORSE CHESTNUT 30 [hp_C]/1 mL; HAMAMELIS VIRGINIANA ROOT BARK/STEM BARK 30 [hp_C]/1 mL; ALOE 30 [hp_C]/1 mL; TRIBASIC CALCIUM PHOSPHATE 30 [hp_C]/1 mL; ACTIVATED CHARCOAL 30 [hp_C]/1 mL; CARBO ANIMALIS 30 [hp_C]/1 mL; LACHESIS MUTA VENOM 30 [hp_C]/1 mL; LYCOPODIUM CLAVATUM SPORE 30 [hp_C]/1 mL; HYDROCHLORIC ACID 30 [hp_C]/1 mL; NITRIC ACID 30 [hp_C]/1 mL; STRYCHNOS NUX-VOMICA SEED 30 [hp_C]/1 mL; PAEONIA OFFICINALIS ROOT 30 [hp_C]/1 mL; KRAMERIA LAPPACEA ROOT 30 [hp_C]/1 mL; SEPIA OFFICINALIS JUICE 30 [hp_C]/1 mL; SULFUR 30 [hp_C]/1 mL
INACTIVE INGREDIENTS: ALCOHOL; WATER

Hemorrhoid

ACTIVE INGREDIENT

ACTIVE INGREDIENTS (*HPUS) - equal amounts of: Aesculus Hipp 4X, 30C, Hamamelis 4X, 30C, Aloe 30C, Calc Phos 30C, Carbo An 30C, Carbo Veg 30C, Lachesis 30C, Lycopodium 30C, Muriaticum Ac 30C, Nitricum Ac 30C, Nux Vom 30C, Paeonia 30C, Ratanhia 30C, Sepia 30C, Sulphur 30C

INDICATIONS AND USAGE

USES: Temporarily relieves burning, bleeding, painful, itching hemorrhoids.**

PURPOSE

USES: Temporarily relieves burning, bleeding, painful, itching hemorrhoids.**

DOSAGE AND ADMINISTRATION

DIRECTIONS: Adults & children above 12 years: 10 drops orally 3 times daily, or as directed by a health care professional.

KEEP OUT OF REACH OF CHILDREN

KEEP OUT OF THE REACH OF CHILDREN. In case of overdose (or accidental ingestion) get medical help or contact a Poison Control Center right away.

WARNINGS:

- Consult a physician for use in children under 12 years of age.
- IF PREGNANT OR BREAST-FEEDING, ask a health care professional before use.
- KEEP OUT OF THE REACH OF CHILDREN. In case of overdose (or accidental ingestion) get medical help or contact a Poison Control Center right away.
- Do not use if TAMPER EVIDENT seal is broken or missing.

INACTIVE INGREDIENTS: Ethyl Alcohol USP, Purified Water

QUESTIONS & COMMENTS?

Natural Creations, Inc. / Woodbine, IA 51579 / 712-647-1600

REFERENCES

*The letters "HPUS" indicate the components in the product are officially monographed in the Homeopathic Pharmacopeia of the United States.

**Claims based on traditional homeopathic practice, not accepted medical evidence. Not FDA evaluated.

PACKAGE LABEL

NDC:43406-0681-1

Hemorrhoid

HOMEOPATHIC

1 fl oz (30mL) / 20% Alcohol